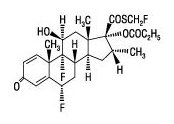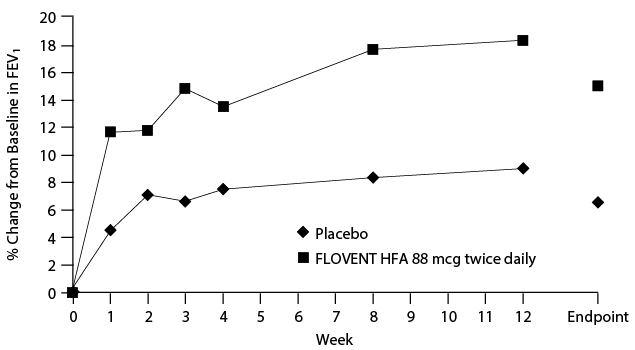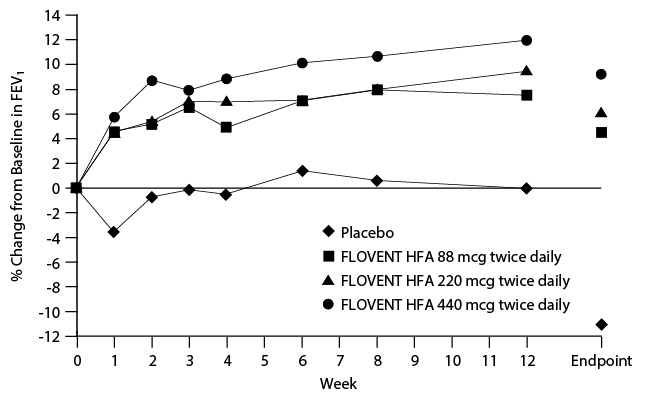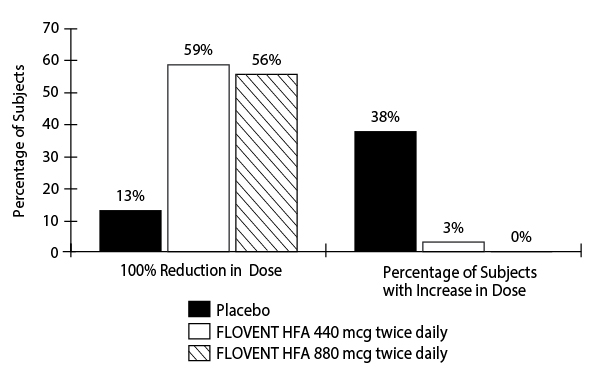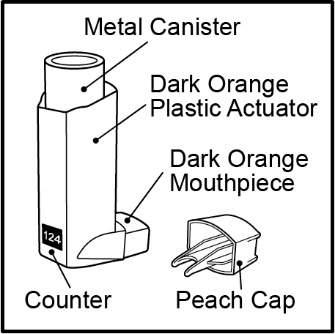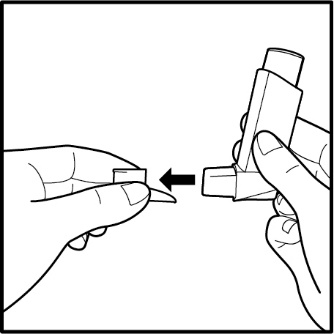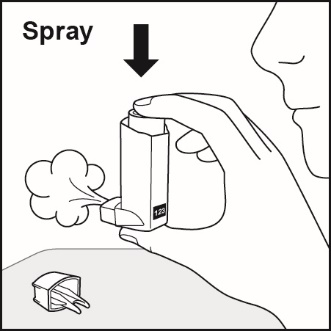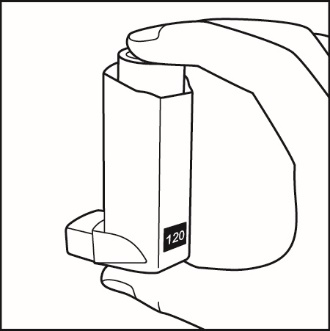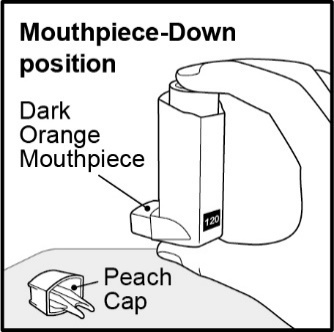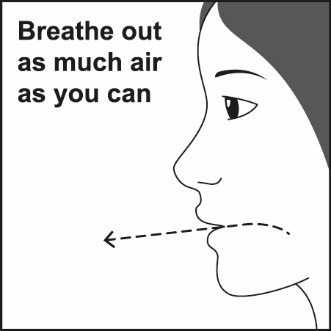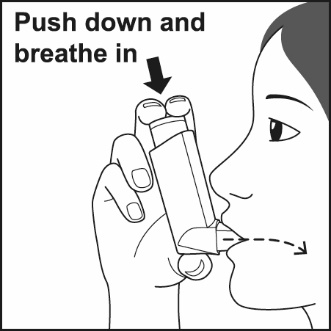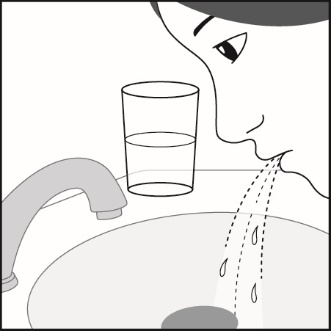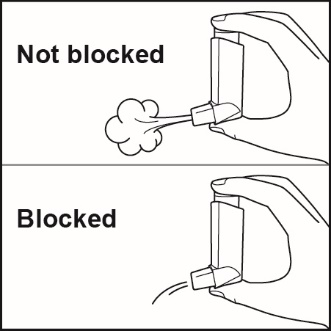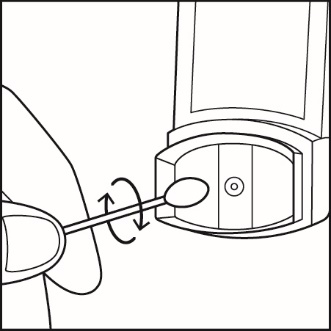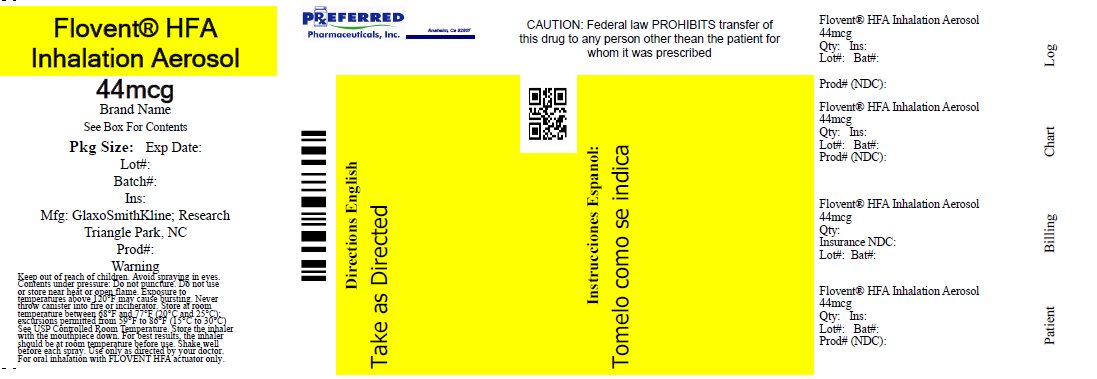 DRUG LABEL: FLOVENT
NDC: 68788-6926 | Form: AEROSOL, METERED
Manufacturer: Preferred Pharmaceuticals Inc.
Category: prescription | Type: HUMAN PRESCRIPTION DRUG LABEL
Date: 20240424

ACTIVE INGREDIENTS: FLUTICASONE PROPIONATE 44 ug/1 1
INACTIVE INGREDIENTS: NORFLURANE

HIGHLIGHTS OF PRESCRIBING INFORMATION

These highlights do not include all the information needed to use FLOVENT HFA safely and effectively. See full prescribing information for FLOVENT HFA.
FLOVENT HFA (fluticasone propionate inhalation aerosol), for oral inhalation use
Initial U.S. Approval: 1994

1 INDICATIONS AND USAGE

FLOVENT HFA is an inhaled corticosteroid indicated for:

- Maintenance treatment of asthma as prophylactic therapy in adult and pediatric patients aged 4 years and older. (1)

Limitations of use: Not indicated for relief of acute bronchospasm. (1)

2 DOSAGE AND ADMINISTRATION

- For oral inhalation only. (2.1)
- Starting dosage is based on prior asthma therapy and disease severity. (2.2)
- Adult and adolescent patients aged 12 years and older: 88 mcg twice daily up to a maximum dosage of 880 mcg twice daily. (2.2)
- Pediatric patients aged 4 to 11 years: 88 mcg twice daily. (Error! Hyperlink reference not valid.)

3 DOSAGE FORMS AND STRENGTHS

Inhalation aerosol:

- 44 mcg fluticasone propionate per actuation (3)
- 110 mcg fluticasone propionate per actuation (3)
- 220 mcg fluticasone propionate per actuation (3)

4 CONTRAINDICATIONS

- Primary treatment of status asthmaticus or acute episodes of asthma requiring intensive measures. (4)
- Hypersensitivity to any ingredient. (4)

5 WARNINGS AND PRECAUTIONS

- Candida albicans infection of the mouth and pharynx may occur. Monitor patients periodically. Advise the patient to rinse his/her mouth with water without swallowing after inhalation to help reduce the risk. (5.1)
- Potential worsening of infections (e.g., existing tuberculosis; fungal, bacterial, viral, or parasitic infections; ocular herpes simplex). Use with caution in patients with these infections. More serious or even fatal course of chickenpox or measles can occur in susceptible patients. (5.3)
- Risk of impaired adrenal function when transferring from systemic corticosteroids. Taper patients slowly from systemic corticosteroids if transferring to FLOVENT HFA. (5.4)
- Hypercorticism and adrenal suppression may occur with very high dosages or at the regular dosage in susceptible individuals. If such changes occur, discontinue FLOVENT HFA slowly. (5.5)
- Assess for decrease in bone mineral density initially and periodically thereafter. (5.7)
- Monitor growth of pediatric patients. (5.8)
- Glaucoma and cataracts may occur with long-term use of an inhaled corticosteroid (ICS). Consider referral to an ophthalmologist in patients who develop ocular symptoms or use FLOVENT HFA long term. (5.9)

6 ADVERSE REACTIONS

Most common adverse reactions (incidence >3%) are upper respiratory tract infection or inflammation, throat irritation, sinusitis, dysphonia, candidiasis, cough, bronchitis, and headache. (6.1)

To report SUSPECTED ADVERSE REACTIONS, contact GlaxoSmithKline at 1-888-825-5249 or FDA at 1-800-FDA-1088 or www.fda.gov/medwatch.

7 DRUG INTERACTIONS

Strong cytochrome P450 3A4 inhibitors (e.g., ritonavir, ketoconazole): Use not recommended. May increase risk of systemic corticosteroid effects. (7.1)

8 USE IN SPECIFIC POPULATIONS

Hepatic impairment: Monitor patients for signs of increased drug exposure. Error! Hyperlink reference not valid.

FULL PRESCRIBING INFORMATION

1 INDICATIONS AND USAGE

FLOVENT HFA is indicated for the maintenance treatment of asthma as prophylactic therapy in adult and pediatric patients aged 4 years and older.

Limitations of Use

FLOVENT HFA is not indicated for the relief of acute bronchospasm.

2 DOSAGE AND ADMINISTRATION

2.1 Administration Information

FLOVENT HFA should be administered by the orally inhaled route only. After inhalation, rinse mouth with water without swallowing to help reduce the risk of oropharyngeal candidiasis.

A valved holding chamber and mask may be used to deliver FLOVENT HFA to young patients.

Priming

Prime FLOVENT HFA before using for the first time by releasing 4 sprays into the air away from the face, shaking well for 5 seconds before each spray. In cases where the inhaler has not been used for more than 7 days or when it has been dropped, prime the inhaler again by shaking well for 5 seconds and releasing 1 spray into the air away from the face. Avoid spraying in eyes.

2.2 Recommended Dosage

Adult and Adolescent Patients Aged 12 Years and Older

The recommended starting dosage for patients aged 12 years and older who are not on an inhaled corticosteroid (ICS): 88 mcg (2 inhalations of 44 mcg fluticasone propionate) twice daily by oral inhalation, approximately 12 hours apart.

- The maximum recommended dosage for patients aged 12 years and older is 880 mcg twice daily.

Pediatric Patients Aged 4 to 11 Years

The recommended dosage for patients aged 4 to 11 years: 88 mcg (2 inhalations of 44 mcg fluticasone propionate) twice daily by oral inhalation, approximately 12 hours apart.

General Dosing Recommendations

The starting dosage is based on previous asthma therapy and asthma severity, including consideration of patients’ current control of asthma symptoms and risk of future exacerbation.

If symptoms arise between doses, an inhaled short-acting beta2-agonist should be used for immediate relief.

Individual patients will experience a variable time to onset and degree of symptom relief. Maximum benefit may not be achieved for 1 to 2 weeks or longer after starting treatment.

For other patients, and for patients who do not respond adequately to the starting dosage after 2 weeks of therapy, higher dosages may provide additional asthma control.

If a dosage regimen fails to provide adequate control of asthma, the therapeutic regimen should be re-evaluated and additional therapeutic options, e.g., replacing the current strength with a higher strength, initiating an ICS and long-acting beta2-agonist (LABA) combination product, or initiating oral corticosteroids, should be considered.

After asthma stability has been achieved, titrate to the lowest effective dosage to reduce the possibility of side effects.

3 DOSAGE FORMS AND STRENGTHS

Inhalation aerosol: dark orange plastic inhaler with a peach cap containing a pressurized metered-dose aerosol canister containing 120 metered inhalations and fitted with a counter.

- 44 mcg of fluticasone propionate from the mouthpiece per actuation
- 110 mcg of fluticasone propionate from the mouthpiece per actuation
- 220 mcg of fluticasone propionate from the mouthpiece per actuation

4 CONTRAINDICATIONS

FLOVENT HFA is contraindicated in the following conditions:

- Primary treatment of status asthmaticus or other acute episodes of asthma where intensive measures are required [see Warnings and Precautions (5.2)].
- Hypersensitivity to any of the ingredients [see Warnings and Precautions (5.6), Adverse Reactions (6.2), Description (11)].

5 WARNINGS AND PRECAUTIONS

5.1 Oropharyngeal Candidiasis

In clinical trials, the development of localized infections of the mouth and pharynx with Candida albicans has occurred in subjects treated with FLOVENT HFA. When such an infection develops, it should be treated with appropriate local or systemic (i.e., oral) antifungal therapy while treatment with FLOVENT HFA continues, but at times therapy with FLOVENT HFA may need to be interrupted. Advise the patient to rinse his/her mouth with water without swallowing following inhalation to help reduce the risk of oropharyngeal candidiasis.

5.2 Acute Asthma Episodes

FLOVENT HFA is not to be regarded as a bronchodilator and is not indicated for rapid relief of bronchospasm. Patients should be instructed to contact their physicians immediately when episodes of asthma that are not responsive to bronchodilators occur during the course of treatment with FLOVENT HFA. During such episodes, patients may require therapy with oral corticosteroids.

5.3 Immunosuppression and Risk of Infections

Persons who are using drugs that suppress the immune system are more susceptible to infections than healthy individuals. Chickenpox and measles, for example, can have a more serious or even fatal course in susceptible children or adults using corticosteroids. In such children or adults who have not had these diseases or been properly immunized, particular care should be taken to avoid exposure. How the dose, route, and duration of corticosteroid administration affect the risk of developing a disseminated infection is not known. The contribution of the underlying disease and/or prior corticosteroid treatment to the risk is also not known. If a patient is exposed to chickenpox, prophylaxis with varicella zoster immune globulin (VZIG) may be indicated. If a patient is exposed to measles, prophylaxis with pooled intramuscular immunoglobulin (IG) may be indicated. (See the respective package inserts for complete VZIG and IG prescribing information.) If chickenpox develops, treatment with antiviral agents may be considered.

ICS should be used with caution, if at all, in patients with active or quiescent tuberculosis infections of the respiratory tract; systemic fungal, bacterial, viral, or parasitic infections; or ocular herpes simplex.

5.4 Transferring Patients from Systemic Corticosteroid Therapy

Hypothalamic-Pituitary-Adrenal Suppression/Adrenal Insufficiency

Particular care is needed for patients who have been transferred from systemically active corticosteroids to ICS because deaths due to adrenal insufficiency have occurred in patients with asthma during and after transfer from systemic corticosteroids to less systemically available ICS. After withdrawal from systemic corticosteroids, a number of months are required for recovery of hypothalamic-pituitary-adrenal (HPA) function.

Patients who have been previously maintained on 20 mg or more of prednisone (or its equivalent) may be most susceptible, particularly when their systemic corticosteroids have been almost completely withdrawn. During this period of HPA suppression, patients may exhibit signs and symptoms of adrenal insufficiency when exposed to trauma, surgery, or infection (particularly gastroenteritis) or other conditions associated with severe electrolyte loss. Although FLOVENT HFA may control asthma symptoms during these episodes, in recommended doses it supplies less than normal physiological amounts of glucocorticoid systemically and does NOT provide the mineralocorticoid activity that is necessary for coping with these emergencies.

During periods of stress or a severe asthma attack, patients who have been withdrawn from systemic corticosteroids should be instructed to resume oral corticosteroids (in large doses) immediately and to contact their physicians for further instruction. These patients should also be instructed to carry a warning card indicating that they may need supplementary systemic corticosteroids during periods of stress or a severe asthma attack.

Patients requiring oral corticosteroids should be weaned slowly from systemic corticosteroid use after transferring to FLOVENT HFA. Prednisone reduction can be accomplished by reducing the daily prednisone dose by 2.5 mg on a weekly basis during therapy with FLOVENT HFA. Lung function (mean forced expiratory volume in 1 second [FEV1] or morning peak expiratory flow [AM PEF]), beta-agonist use, and asthma symptoms should be carefully monitored during withdrawal of oral corticosteroids. In addition, patients should be observed for signs and symptoms of adrenal insufficiency, such as fatigue, lassitude, weakness, nausea and vomiting, and hypotension.

Unmasking of Allergic Conditions Previously Suppressed by Systemic Corticosteroids

Transfer of patients from systemic corticosteroid therapy to FLOVENT HFA may unmask allergic conditions previously suppressed by the systemic corticosteroid therapy (e.g., rhinitis, conjunctivitis, eczema, arthritis, eosinophilic conditions).

Corticosteroid Withdrawal Symptoms

During withdrawal from oral corticosteroids, some patients may experience symptoms of systemically active corticosteroid withdrawal (e.g., joint and/or muscular pain, lassitude, depression) despite maintenance or even improvement of respiratory function.

5.5 Hypercorticism and Adrenal Suppression

Fluticasone propionate will often help control asthma symptoms with less suppression of HPA function than therapeutically equivalent oral doses of prednisone. Since fluticasone propionate is absorbed into the circulation and can be systemically active at higher doses, the beneficial effects of FLOVENT HFA in minimizing HPA dysfunction may be expected only when recommended dosages are not exceeded and individual patients are titrated to the lowest effective dose. A relationship between plasma levels of fluticasone propionate and inhibitory effects on stimulated cortisol production has been shown after 4 weeks of treatment with fluticasone propionate inhalation aerosol. Since individual sensitivity to effects on cortisol production exists, physicians should consider this information when prescribing FLOVENT HFA.

Because of the possibility of significant systemic absorption of ICS in sensitive patients, patients treated with FLOVENT HFA should be observed carefully for any evidence of systemic corticosteroid effects. Particular care should be taken in observing patients postoperatively or during periods of stress for evidence of inadequate adrenal response.

It is possible that systemic corticosteroid effects such as hypercorticism and adrenal suppression (including adrenal crisis) may appear in a small number of patients who are sensitive to these effects. If such effects occur, FLOVENT HFA should be reduced slowly, consistent with accepted procedures for reducing systemic corticosteroids, and other treatments for management of asthma symptoms should be considered.

5.6 Hypersensitivity Reactions, including Anaphylaxis

Immediate hypersensitivity reactions (e.g., urticaria, angioedema, rash, bronchospasm, hypotension), including anaphylaxis, may occur after administration of FLOVENT HFA [see Contraindications (4)].

5.7 Reduction in Bone Mineral Density

Decreases in bone mineral density (BMD) have been observed with long-term administration of products containing ICS. The clinical significance of small changes in BMD with regard to long-term consequences such as fracture is unknown. Patients with major risk factors for decreased bone mineral content, such as prolonged immobilization, family history of osteoporosis, postmenopausal status, tobacco use, advanced age, poor nutrition, or chronic use of drugs that can reduce bone mass (e.g., anticonvulsants, oral corticosteroids), should be monitored and treated with established standards of care.

A 2-year trial in 160 subjects (females aged 18 to 40 years, males 18 to 50) with asthma receiving chlorofluorocarbon (CFC)-propelled fluticasone propionate inhalation aerosol 88 or 440 mcg twice daily demonstrated no statistically significant changes in BMD at any time point (24, 52, 76, and 104 weeks of double-blind treatment) as assessed by dual-energy x-ray absorptiometry at lumbar regions L1 through L4.

5.8 Effect on Growth

Orally inhaled corticosteroids may cause a reduction in growth velocity when administered to pediatric patients. Monitor the growth of pediatric patients receiving FLOVENT HFA routinely (e.g., via stadiometry). To minimize the systemic effects of orally inhaled corticosteroids, including FLOVENT HFA, titrate each patient’s dosage to the lowest dosage that effectively controls his/her symptoms [see Dosage and Administration (2.2), Use in Specific Populations (8.4)].

5.9 Glaucoma and Cataracts

Glaucoma, increased intraocular pressure, and cataracts have been reported in patients following the long-term administration of ICS, including fluticasone propionate. Consider referral to an ophthalmologist in patients who develop ocular symptoms or use FLOVENT HFA long term.

5.10 Paradoxical Bronchospasm

As with other inhaled medicines, bronchospasm may occur with an immediate increase in wheezing after dosing. If bronchospasm occurs following dosing with FLOVENT HFA, it should be treated immediately with an inhaled, short-acting bronchodilator; FLOVENT HFA should be discontinued immediately; and alternative therapy should be instituted.

5.11 Drug Interactions with Strong Cytochrome P450 3A4 Inhibitors

The use of strong cytochrome P450 3A4 (CYP3A4) inhibitors (e.g., ritonavir, atazanavir, clarithromycin, indinavir, itraconazole, nefazodone, nelfinavir, saquinavir, ketoconazole, telithromycin) with FLOVENT HFA is not recommended because increased systemic corticosteroid adverse effects may occur [see Drug Interactions (7.1), Clinical Pharmacology (12.3)].

5.12 Eosinophilic Conditions and Churg-Strauss Syndrome

In rare cases, patients on inhaled fluticasone propionate may present with systemic eosinophilic conditions. Some of these patients have clinical features of vasculitis consistent with Churg-Strauss syndrome, a condition that is often treated with systemic corticosteroid therapy. These events usually, but not always, have been associated with the reduction and/or withdrawal of oral corticosteroid therapy following the introduction of fluticasone propionate. Cases of serious eosinophilic conditions have also been reported with other ICS in this clinical setting. Physicians should be alert to eosinophilia, vasculitic rash, worsening pulmonary symptoms, cardiac complications, and/or neuropathy presenting in their patients. A causal relationship between fluticasone propionate and these underlying conditions has not been established.

6 ADVERSE REACTIONS

The following clinically significant adverse reactions are described elsewhere in the labeling:

- Oropharyngeal candidiasis infection [see Warnings and Precautions (5.1)]
- Immunosuppression and risk of infections [see Warnings and Precautions (5.3)]
- Hypercorticism and adrenal suppression [see Warnings and Precautions (5.5)]
- Reduction in bone mineral density [see Warnings and Precautions (5.7)]
- Growth effects [see Warnings and Precautions (5.8)]
- Glaucoma and cataracts [see Warnings and Precautions (5.9)]

6.1 Clinical Trials Experience

Because clinical trials are conducted under widely varying conditions, adverse reaction rates observed in the clinical trials of a drug cannot be directly compared with rates in the clinical trials of another drug and may not reflect the rates observed in practice.

The incidence of common adverse reactions in Table 1 is based upon 2 placebo-controlled U.S. clinical trials in which 812 adult and adolescent subjects (457 females and 355 males) previously treated with as-needed bronchodilators and/or ICS were treated twice daily for up to 12 weeks with 2 inhalations of FLOVENT HFA 44 mcg, FLOVENT HFA 110 mcg, FLOVENT HFA 220 mcg (dosages of 88, 220, or 440 mcg twice daily), or placebo.

Table 1. Adverse Reactions with FLOVENT HFA with >3% Incidence and More Common than Placebo in Subjects Aged 12 Years and Older with Asthma
Adverse Event | FLOVENT HFA; 88 mcg; Twice Daily; (n = 203); % | FLOVENT HFA; 220 mcg; Twice Daily; (n = 204); % | FLOVENT HFA; 440 mcg; Twice Daily; (n = 202); % | Placebo; (n = 203); %
Ear, nose, and throat
Upper respiratory tract infection | 18 | 16 | 16 | 14
Throat irritation | 8 | 8 | 10 | 5
Upper respiratory inflammation | 2 | 5 | 5 | 1
Sinusitis/sinus infection | 6 | 7 | 4 | 3
Hoarseness/dysphonia | 2 | 3 | 6 | <1
Gastrointestinal
Candidiasis mouth/throat and non-site specific | 4 | 2 | 5 | <1
Lower respiratory
Cough | 4 | 6 | 4 | 5
Bronchitis | 2 | 2 | 6 | 5
Neurological
Headache | 11 | 7 | 5 | 6

Table 1 includes all events (whether considered drug-related or nondrug-related by the investigator) that occurred at a rate of over 3% in any of the groups treated with FLOVENT HFA and were more common than in the placebo group. Less than 2% of subjects discontinued from the trials because of adverse reactions. The average duration of exposure was 73 to 76 days in the active treatment groups compared with 60 days in the placebo group.

Additional Adverse Reactions

Other adverse reactions not previously listed, whether considered drug-related or not by the investigators, that were reported more frequently by subjects with asthma treated with FLOVENT HFA compared with subjects treated with placebo include the following: rhinitis, rhinorrhea/post-nasal drip, nasal sinus disorders, laryngitis, diarrhea, viral gastrointestinal infections, dyspeptic symptoms, gastrointestinal discomfort and pain, hyposalivation, musculoskeletal pain, muscle pain, muscle stiffness/tightness/rigidity, dizziness, migraines, fever, viral infections, pain, chest symptoms, viral skin infections, muscle injuries, soft tissue injuries, urinary infections.

Fluticasone propionate inhalation aerosol (440 or 880 mcg twice daily) was administered for 16 weeks to 168 subjects with asthma requiring oral corticosteroids (Trial 3). Adverse reactions not included above but reported by more than 3 subjects in either group treated with FLOVENT HFA and more commonly than in the placebo group included nausea and vomiting, arthralgia and articular rheumatism, and malaise and fatigue.

In 2 long-term trials (26 and 52 weeks), the pattern of adverse reactions in subjects treated with FLOVENT HFA at dosages up to 440 mcg twice daily was similar to that observed in the 12-week trials. There were no new and/or unexpected adverse reactions with long-term treatment.

Pediatric Subjects Aged 4 to 11 Years

FLOVENT HFA has been evaluated for safety in 56 pediatric subjects who received 88 mcg twice daily for 4 weeks. Types of adverse reactions in these pediatric subjects were generally similar to those observed in adults and adolescents.

6.2 Postmarketing Experience

In addition to adverse reactions reported from clinical trials, the following adverse reactions have been identified during postapproval use of fluticasone propionate. Because these reactions are reported voluntarily from a population of uncertain size, it is not always possible to reliably estimate their frequency or establish a causal relationship to drug exposure. These events have been chosen for inclusion due to either their seriousness, frequency of reporting, or causal connection to fluticasone propionate or a combination of these factors.

Ear, Nose, and Throat

Aphonia, facial and oropharyngeal edema, and throat soreness and irritation.

Endocrine and Metabolic

Cushingoid features, growth velocity reduction in children/adolescents, hyperglycemia, osteoporosis, and weight gain.

Eye

Cataracts.

Gastrointestinal Disorders

Dental caries and tooth discoloration.

Immune System Disorders

Immediate and delayed hypersensitivity reactions, including urticaria, anaphylaxis, rash, and angioedema and bronchospasm, have been reported.

Infections and Infestations

Esophageal candidiasis.

Psychiatry

Agitation, aggression, anxiety, depression, and restlessness. Behavioral changes, including hyperactivity and irritability, have been reported very rarely and primarily in children.

Respiratory

Asthma exacerbation, chest tightness, cough, dyspnea, immediate and delayed bronchospasm, paradoxical bronchospasm, pneumonia, and wheeze.

Skin

Contusions, cutaneous hypersensitivity reactions, ecchymoses, and pruritus.

7 DRUG INTERACTIONS

7.1 Inhibitors of Cytochrome P450 3A4

Fluticasone propionate is a substrate of CYP3A4. The use of strong CYP3A4 inhibitors (e.g., ritonavir, atazanavir, clarithromycin, indinavir, itraconazole, nefazodone, nelfinavir, saquinavir, ketoconazole, telithromycin) with FLOVENT HFA is not recommended because increased systemic corticosteroid adverse effects may occur.

Ritonavir

A drug interaction trial with fluticasone propionate aqueous nasal spray in healthy subjects has shown that ritonavir (a strong CYP3A4 inhibitor) can significantly increase plasma fluticasone propionate exposure, resulting in significantly reduced serum cortisol concentrations [see Clinical Pharmacology (12.3)]. During postmarketing use, there have been reports of clinically significant drug interactions in patients receiving fluticasone propionate and ritonavir, resulting in systemic corticosteroid effects including Cushing’s syndrome and adrenal suppression.

Ketoconazole

Coadministration of orally inhaled fluticasone propionate (1,000 mcg) and ketoconazole (200 mg once daily) resulted in a 1.9-fold increase in plasma fluticasone propionate exposure and a 45% decrease in plasma cortisol area under the curve (AUC), but had no effect on urinary excretion of cortisol.

8 USE IN SPECIFIC POPULATIONS

8.1 Pregnancy

Risk Summary

There are insufficient data on the use of FLOVENT HFA in pregnant women. There are clinical considerations with the use of FLOVENT HFA in pregnant women. (See Clinical Considerations.) In animals, teratogenicity characteristic of corticosteroids, decreased fetal body weight and/or skeletal variations in rats, mice, and rabbits, was observed with subcutaneously administered maternal toxic doses of fluticasone propionate less than the maximum recommended human daily inhaled dose (MRHDID) on a mcg/m^2 basis. (See Data.) However, fluticasone propionate administered via inhalation to rats decreased fetal body weight but did not induce teratogenicity at a maternal toxic dose less than the MRHDID on a mcg/m^2 basis. (See Data.) Experience with oral corticosteroids suggests that rodents are more prone to teratogenic effects from corticosteroids than humans.

The estimated risk of major birth defects and miscarriage for the indicated population is unknown. In the U.S. general population, the estimated risk of major birth defects and miscarriage in clinically recognized pregnancies is 2% to 4% and 15% to 20%, respectively.

Clinical Considerations

Disease-Associated Maternal and/or Embryofetal Risk: In women with poorly or moderately controlled asthma, there is an increased risk of several perinatal outcomes such as pre-eclampsia in the mother and prematurity, low birth weight, and small for gestational age in the neonate. Pregnant women with asthma should be closely monitored and medication adjusted as necessary to maintain optimal asthma control.

Data

Human Data: Following inhaled administration, fluticasone propionate was detected in the neonatal cord blood after delivery.

Animal Data: In embryofetal development studies with pregnant rats and mice dosed by the subcutaneous route throughout the period of organogenesis, fluticasone propionate was teratogenic in both species. Omphalocele, decreased body weight, and skeletal variations were observed in rat fetuses, in the presence of maternal toxicity, at a dose approximately 0.5 times the MRHDID (on a mcg/m^2 basis with a maternal subcutaneous dose of 100 mcg/kg/day). The rat no observed adverse effect level (NOAEL) was observed at approximately 0.17 times the MRHDID (on a mcg/m^2 basis with a maternal subcutaneous dose of 30 mcg/kg/day). Cleft palate and fetal skeletal variations were observed in mouse fetuses at a dose approximately 0.1 times the MRHDID (on a mcg/m^2 basis with a maternal subcutaneous dose of 45 mcg/kg/day). The mouse NOAEL was observed with a dose approximately 0.04 times the MRHDID (on a mcg/m^2 basis with a maternal subcutaneous dose of 15 mcg/kg/day).

In an embryofetal development study with pregnant rats dosed by the inhalation route throughout the period of organogenesis, fluticasone propionate produced decreased fetal body weights and skeletal variations, in the presence of maternal toxicity, at a dose approximately 0.14 times the MRHDID (on a mcg/m^2 basis with a maternal inhalation dose of 25.7 mcg/kg/day); however, there was no evidence of teratogenicity. The NOAEL was observed with a dose approximately 0.03 times the MRHDID (on a mcg/m^2 basis with a maternal inhalation dose of 5.5 mcg/kg/day).

In an embryofetal development study in pregnant rabbits that were dosed by the subcutaneous route throughout organogenesis, fluticasone propionate produced reductions of fetal body weights, in the presence of maternal toxicity, at doses approximately 0.006 times the MRHDID and higher (on a mcg/m^2 basis with a maternal subcutaneous dose of 0.57 mcg/kg/day). Teratogenicity was evident based upon a finding of cleft palate for 1 fetus at a dose approximately 0.04 times the MRHDID (on a mcg/m^2 basis with a maternal subcutaneous dose of 4 mcg/kg/day). The NOAEL was observed in rabbit fetuses with a dose approximately 0.001 times the MRHDID (on a mcg/m^2 basis with a maternal subcutaneous dose of 0.08 mcg/kg/day).

Fluticasone propionate crossed the placenta following subcutaneous administration to mice and rats and oral administration to rabbits.

In a pre- and post-natal development study in pregnant rats dosed from late gestation through delivery and lactation (Gestation Day 17 to Postpartum Day 22), fluticasone propionate was not associated with decreases in pup body weight, and had no effects on developmental landmarks, learning, memory, reflexes, or fertility at doses up to 0.3 times the MRHDID (on a mcg/m^2 basis with maternal subcutaneous doses up to 50 mcg/kg/day).

8.2 Lactation

Risk Summary

There are no available data on the presence of fluticasone propionate in human milk, the effects on the breastfed child, or the effects on milk production. Other corticosteroids have been detected in human milk. However, fluticasone propionate concentrations in plasma after inhaled therapeutic doses are low and therefore concentrations in human breast milk are likely to be correspondingly low [see Clinical Pharmacology (12.3)]. The developmental and health benefits of breastfeeding should be considered along with the mother’s clinical need for FLOVENT HFA and any potential adverse effects on the breastfed child from FLOVENT HFA or from the underlying maternal condition.

Data

Animal Data: Subcutaneous administration of tritiated fluticasone propionate at a dose of 10 mcg/kg/day to lactating rats resulted in measurable levels in milk.

8.4 Pediatric Use

The safety and effectiveness of FLOVENT HFA in pediatric patients aged 4 years and older have been established [see Adverse Reactions (6.1), Clinical Pharmacology (Error! Hyperlink reference not valid.), Clinical Studies (Error! Hyperlink reference not valid.)]. Use of FLOVENT HFA in patients aged 4 to 11 years is supported by evidence from adequate and well-controlled trials in adults and adolescents aged 12 years and older, pharmacokinetic trials in patients aged 4 to 11 years, established efficacy of fluticasone propionate formulated as FLOVENT DISKUS (fluticasone propionate inhalation powder) and FLOVENT ROTADISK (fluticasone propionate inhalation powder) in patients aged 4 to 11 years, and supportive findings with FLOVENT HFA in a trial conducted in subjects aged 4 to 11 years.

The safety and effectiveness of FLOVENT HFA in pediatric patients younger than 4 years have not been established.

Effects on Growth

Orally inhaled corticosteroids may cause a reduction in growth velocity when administered to pediatric patients. A reduction of growth velocity in children or teenagers may occur as a result of poorly controlled asthma or from use of corticosteroids including ICS. The effects of long-term treatment of children and adolescents with ICS, including fluticasone propionate, on final adult height are not known.

Controlled clinical trials have shown that ICS may cause a reduction in growth in pediatric patients. In these trials, the mean reduction in growth velocity was approximately 1 cm/year (range: 0.3 to 1.8 cm/year) and appeared to depend upon dose and duration of exposure. This effect was observed in the absence of laboratory evidence of HPA axis suppression, suggesting that growth velocity is a more sensitive indicator of systemic corticosteroid exposure in pediatric patients than some commonly used tests of HPA axis function. The long-term effects of this reduction in growth velocity associated with orally inhaled corticosteroids, including the impact on final adult height, are unknown. The potential for “catch-up” growth following discontinuation of treatment with orally inhaled corticosteroids has not been adequately studied. The effects on growth velocity of treatment with orally inhaled corticosteroids for over 1 year, including the impact on final adult height, are unknown. The growth of children and adolescents receiving orally inhaled corticosteroids, including FLOVENT HFA, should be monitored routinely (e.g., via stadiometry). The potential growth effects of prolonged treatment should be weighed against the clinical benefits obtained and the risks associated with alternative therapies. To minimize the systemic effects of orally inhaled corticosteroids, including FLOVENT HFA, each patient should be titrated to the lowest dose that effectively controls his/her symptoms.

Since a cross trial comparison in adult and adolescent subjects (aged 12 years and older) indicated that systemic exposure of inhaled fluticasone propionate from FLOVENT HFA would be higher than exposure from FLOVENT ROTADISK, results from a trial to assess the potential growth effects of FLOVENT ROTADISK in pediatric subjects (aged 4 to 11 years) are provided.

A 52-week placebo-controlled trial to assess the potential growth effects of fluticasone propionate inhalation powder (FLOVENT ROTADISK) at 50 and 100 mcg twice daily was conducted in the U.S. in 325 prepubescent children (244 males and 81 females) aged 4 to 11 years. The mean growth velocities at 52 weeks observed in the intent-to-treat population were 6.32 cm/year in the placebo group (n = 76), 6.07 cm/year in the 50-mcg group (n = 98), and 5.66 cm/year in the 100-mcg group (n = 89). An imbalance in the proportion of children entering puberty between groups and a higher dropout rate in the placebo group due to poorly controlled asthma may be confounding factors in interpreting these data. A separate subset analysis of children who remained prepubertal during the trial revealed growth rates at 52 weeks of 6.10 cm/year in the placebo group (n = 57), 5.91 cm/year in the 50-mcg group (n = 74), and 5.67 cm/year in the 100-mcg group (n = 79). In children aged 8.5 years, the mean age of children in this trial, the range for expected growth velocity is: boys – 3rd percentile = 3.8 cm/year, 50th percentile = 5.4 cm/year, and 97th percentile = 7.0 cm/year; girls – 3rd percentile = 4.2 cm/year, 50th percentile = 5.7 cm/year, and 97th percentile = 7.3 cm/year. The clinical relevance of these growth data is not certain.

Pediatric Patients Younger than 4 Years

Pharmacokinetics: [see Clinical Pharmacology (12.3)].

Pharmacodynamics: A 12-week, double-blind, placebo-controlled, parallel-group trial was conducted in children with asthma aged 1 to younger than 4 years. Twelve-hour overnight urinary cortisol excretion after a 12-week treatment period with 88 mcg of FLOVENT HFA twice daily (n = 73) and with placebo (n = 42) were calculated. The mean and median change from baseline in urine cortisol over 12 hours were -0.7 and 0.0 mcg for FLOVENT HFA and 0.3 and -0.2 mcg for placebo, respectively.

In a 1-way crossover trial in children aged 6 to younger than 12 months with reactive airways disease (N = 21), serum cortisol was measured over a 12-hour dosing period. Subjects received placebo treatment for a 2-week period followed by a 4-week treatment period with 88 mcg of FLOVENT HFA twice daily with an AeroChamber Plus Valved Holding Chamber (VHC) with mask. The geometric mean ratio of serum cortisol over 12 hours [AUC(0-12 h)] following FLOVENT HFA (n = 16) versus placebo (n = 18) was 0.95 (95% CI: 0.72, 1.27).

Safety: FLOVENT HFA administered as 88 mcg twice daily was evaluated for safety in 239 pediatric subjects aged 1 to younger than 4 years in a 12-week, double-blind, placebo-controlled trial. Treatments were administered with an AeroChamber Plus VHC with mask. The following events occurred with a frequency >3% and more frequently in subjects receiving FLOVENT HFA than in subjects receiving placebo, regardless of causality assessment: pyrexia, nasopharyngitis, upper respiratory tract infection, vomiting, otitis media, diarrhea, bronchitis, pharyngitis, and viral infection.

FLOVENT HFA administered as 88 mcg twice daily was evaluated for safety in 23 pediatric subjects aged 6 to 12 months in an open-label placebo-controlled trial. Treatments were administered with an AeroChamber Plus VHC with mask for 2 weeks with placebo followed by 4 weeks with active drug. There was no discernable difference in the types of adverse events reported between subjects receiving placebo compared with the active drug.

In Vitro Testing of Dose Delivery with Holding Chambers: In vitro dose characterization studies were performed to evaluate the delivery of FLOVENT HFA via holding chambers with attached masks. The studies were conducted with 2 different holding chambers (AeroChamber Plus VHC and AeroChamber Z-STAT Plus VHC) with masks (small and medium size) at inspiratory flow rates of 4.9, 8.0, and 12.0 L/min in combination with holding times of 0, 2, 5, and 10 seconds. The flow rates were selected to be representative of inspiratory flow rates of children aged 6 to 12 months, 2 to 5 years, and over 5 years, respectively. The mean delivered dose of fluticasone propionate through the holding chambers with masks was lower than the 44 mcg of fluticasone propionate delivered directly from the actuator mouthpiece. The results were similar through both holding chambers (see Table 2 for data for the AeroChamber Plus VHC). The fine particle fraction (approximately 1 to 5 μm) across the flow rates used in these studies was 70% to 84% of the delivered dose, consistent with the removal of the coarser fraction by the holding chamber. In contrast, the fine particle fraction for FLOVENT HFA delivered without a holding chamber typically represents 42% to 55% of the delivered dose measured at the standard flow rate of 28.3 L/min. These data suggest that, on a per kilogram basis, young children receive a comparable dose of fluticasone propionate when delivered via a holding chamber and mask as adults do without their use.

Table 2. In Vitro Medication Delivery through AeroChamber Plus Valved Holding Chamber with a Mask
Age | Mask | Flow Rate; (L/min) | Holding Time; (seconds) | Mean Medication Delivery through AeroChamber Plus Valved Holding Chamber; (mcg/actuation) | Body Weight 50th Percentile; (kg)a | Medication Delivered per Actuation; (mcg/kg)b
6 to 12 Months | Small | 4.9 | 0 | 8.3 | 7.5-9.9 | 0.8-1.1
 |  |  | 2 | 6.7 |  | 0.7-0.9
 |  |  | 5 | 7.5 |  | 0.8-1.0
 |  |  | 10 | 7.5 |  | 0.8-1.0
2 to 5 Years | Small | 8.0 | 0 | 7.3 | 12.3-18.0 | 0.4-0.6
 |  |  | 2 | 6.8 |  | 0.4-0.6
 |  |  | 5 | 6.7 |  | 0.4-0.5
 |  |  | 10 | 7.7 |  | 0.4-0.6
2 to 5 Years | Medium | 8.0 | 0 | 7.8 | 12.3-18.0 | 0.4-0.6
 |  |  | 2 | 7.7 |  | 0.4-0.6
 |  |  | 5 | 8.1 |  | 0.5-0.7
 |  |  | 10 | 9.0 |  | 0.5-0.7
>5 Years | Medium | 12.0 | 0 | 12.3 | 18.0 | 0.7
 |  |  | 2 | 11.8 |  | 0.7
 |  |  | 5 | 12.0 |  | 0.7
 |  |  | 10 | 10.1 |  | 0.6
a Centers for Disease Control growth charts, developed by the National Center for Health Statistics in collaboration with the National Center for Chronic Disease Prevention and Health Promotion (2000). Ranges correspond to the average of the 50th percentile weight for boys and girls at the ages indicated.
b A single inhalation of FLOVENT HFA in a 70-kg adult without use of a valved holding chamber and mask delivers approximately 44 mcg, or 0.6 mcg/kg.

8.5 Geriatric Use

Of the total number of subjects treated with FLOVENT HFA in U.S. and non-U.S. clinical trials, 173 were aged 65 years or older, 19 of which were 75 years or older. No overall differences in safety or effectiveness were observed between these subjects and younger subjects, and other reported clinical experience has not identified differences in responses between the elderly and younger subjects, but greater sensitivity of some older individuals cannot be ruled out.

8.6 Hepatic Impairment

Formal pharmacokinetic studies using FLOVENT HFA have not been conducted in patients with hepatic impairment. Since fluticasone propionate is predominantly cleared by hepatic metabolism, impairment of liver function may lead to accumulation of fluticasone propionate in plasma. Therefore, patients with hepatic disease should be closely monitored.

8.7 Renal Impairment

Formal pharmacokinetic studies using FLOVENT HFA have not been conducted in patients with renal impairment.

10 OVERDOSAGE

Chronic overdosage may result in signs/symptoms of hypercorticism [see Warnings and Precautions (5.5)].

11 DESCRIPTION

FLOVENT HFA is a pressurized metered dose inhaler for oral inhalation. The active component of FLOVENT HFA 44 mcg, FLOVENT HFA 110 mcg, and FLOVENT HFA 220 mcg is fluticasone propionate, a corticosteroid having the chemical name S-(fluoromethyl) 6α,9-difluoro-11β,17-dihydroxy-16α-methyl-3-oxoandrosta-1,4-diene-17β-carbothioate,17-propionate and the following chemical structure:

Fluticasone propionate is a white powder with a molecular weight of 500.6, and the empirical formula is C25H31F3O5S. It is practically insoluble in water, freely soluble in dimethyl sulfoxide and dimethylformamide, and slightly soluble in methanol and 95% ethanol.

FLOVENT HFA is a dark orange plastic inhaler with a peach cap containing a pressurized metered-dose aerosol canister fitted with a counter. Each canister contains a microcrystalline suspension of micronized fluticasone propionate in propellant HFA-134a (1,1,1,2-tetrafluoroethane). It contains no other excipients.

After priming, each actuation of the inhaler delivers 50, 125, or 250 mcg of fluticasone propionate in 60 mg of suspension (for the 44-mcg product) or in 75 mg of suspension (for the 110- and 220-mcg products) from the valve. Each actuation delivers 44, 110, or 220 mcg of fluticasone propionate from the actuator. The actual amount of drug delivered to the lung will depend on patient factors, such as the coordination between the actuation of the inhaler and inspiration through the delivery system.

Prime FLOVENT HFA before using for the first time by releasing 4 sprays into the air away from the face, shaking well for 5 seconds before each spray. In cases where the inhaler has not been used for more than 7 days or when it has been dropped, prime the inhaler again by shaking well for 5 seconds and releasing 1 spray into the air away from the face. Avoid spraying in eyes.

12 CLINICAL PHARMACOLOGY

12.1 Mechanism of Action

Fluticasone propionate is a synthetic trifluorinated corticosteroid with anti-inflammatory activity. Fluticasone propionate has been shown in vitro to exhibit a binding affinity for the human glucocorticoid receptor that is 18 times that of dexamethasone, almost twice that of beclomethasone‑17‑monopropionate (BMP), the active metabolite of beclomethasone dipropionate, and over 3 times that of budesonide. Data from the McKenzie vasoconstrictor assay in man are consistent with these results. The clinical significance of these findings is unknown.

Inflammation is an important component in the pathogenesis of asthma. Corticosteroids have been shown to have a wide range of actions on multiple cell types (e.g., mast cells, eosinophils, neutrophils, macrophages, lymphocytes) and mediators (e.g., histamine, eicosanoids, leukotrienes, cytokines) involved in inflammation. These anti-inflammatory actions of corticosteroids contribute to their efficacy in asthma.

Though effective for the treatment of asthma, corticosteroids do not affect asthma symptoms immediately. Individual patients will experience a variable time to onset and degree of symptom relief. Maximum benefit may not be achieved for 1 to 2 weeks or longer after starting treatment. When corticosteroids are discontinued, asthma stability may persist for several days or longer.

Trials in subjects with asthma have shown a favorable ratio between topical anti-inflammatory activity and systemic corticosteroid effects with recommended doses of orally inhaled fluticasone propionate. This is explained by a combination of a relatively high local anti-inflammatory effect, negligible oral systemic bioavailability (<1%), and the minimal pharmacological activity of the only metabolite detected in man.

12.2 Pharmacodynamics

Serum cortisol concentrations, urinary excretion of cortisol, and urine 6-β-hydroxycortisol excretion collected over 24 hours in 24 healthy subjects following 8 inhalations of fluticasone propionate HFA 44, 110, and 220 mcg decreased with increasing dose. However, in patients with asthma treated with 2 inhalations of fluticasone propionate HFA 44, 110, and 220 mcg twice daily for at least 4 weeks, differences in serum cortisol AUC(0-12 h) (n = 65) and 24-hour urinary excretion of cortisol (n = 47) compared with placebo were not related to dose and generally not significant. In the trial with healthy volunteers, the effect of propellant was also evaluated by comparing results following the 220-mcg strength inhaler containing HFA 134a propellant with the same strength of inhaler containing CFC 11/12 propellant. A lesser effect on the HPA axis with the HFA formulation was observed for serum cortisol, but not urine cortisol and 6-betahydroxy cortisol excretion. In addition, in a crossover trial in children with asthma aged 4 to 11 years (N = 40), 24-hour urinary excretion of cortisol was not affected after a 4-week treatment period with 88 mcg of fluticasone propionate HFA twice daily compared with urinary excretion after the 2-week placebo period. The ratio (95% CI) of urinary excretion of cortisol over 24 hours following fluticasone propionate HFA versus placebo was 0.987 (0.796, 1.223).

The potential systemic effects of fluticasone propionate HFA on the HPA axis were also studied in subjects with asthma. Fluticasone propionate given by inhalation aerosol at dosages of 440 or 880 mcg twice daily was compared with placebo in oral corticosteroid-dependent subjects with asthma (range of mean dose of prednisone at baseline: 13 to 14 mg/day) in a 16-week trial. Consistent with maintenance treatment with oral corticosteroids, abnormal plasma cortisol responses to short cosyntropin stimulation (peak plasma cortisol <18 mcg/dL) were present at baseline in the majority of subjects participating in this trial (69% of subjects later randomized to placebo and 72% to 78% of subjects later randomized to fluticasone propionate HFA). At week 16, 8 subjects (73%) on placebo compared with 14 (54%) and 13 (68%) subjects receiving fluticasone propionate HFA (440 and 880 mcg twice daily, respectively) had post-stimulation cortisol levels of <18 mcg/dL.

12.3 Pharmacokinetics

Absorption

Fluticasone propionate acts locally in the lung; therefore, plasma levels do not predict therapeutic effect. Trials using oral dosing of labeled and unlabeled drug have demonstrated that the oral systemic bioavailability of fluticasone propionate is negligible (<1%), primarily due to incomplete absorption and presystemic metabolism in the gut and liver. In contrast, the majority of the fluticasone propionate delivered to the lung is systemically absorbed.

Distribution

Following intravenous administration, the initial disposition phase for fluticasone propionate was rapid and consistent with its high lipid solubility and tissue binding. The volume of distribution averaged 4.2 L/kg.

The percentage of fluticasone propionate bound to human plasma proteins averages 99%. Fluticasone propionate is weakly and reversibly bound to erythrocytes and is not significantly bound to human transcortin.

Elimination

Following intravenous dosing, fluticasone propionate showed polyexponential kinetics and had a terminal elimination half-life of approximately 7.8 hours. The total clearance of fluticasone propionate is high (average, 1,093 mL/min), with renal clearance accounting for <0.02% of the total. Less than 5% of a radiolabeled oral dose was excreted in the urine as metabolites, with the remainder excreted in the feces as parent drug and metabolites.

Metabolism: The only circulating metabolite detected in man is the 17β-carboxylic acid derivative of fluticasone propionate, which is formed through the CYP3A4 pathway. This metabolite had less affinity (approximately 1/2,000) than the parent drug for the glucocorticoid receptor of human lung cytosol in vitro and negligible pharmacological activity in animal studies. Other metabolites detected in vitro using cultured human hepatoma cells have not been detected in man.

Specific Populations

Male and Female Patients: No significant difference in clearance (CL/F) of fluticasone propionate was observed.

Pediatric Patients: A population pharmacokinetic analysis was performed for FLOVENT HFA using steady-state data from 4 controlled clinical trials and single-dose data from 1 controlled clinical trial. The combined cohort for analysis included 269 subjects (161 males and 108 females) with asthma aged 6 months to 66 years who received treatment with FLOVENT HFA. Most of these subjects (n = 215) were treated with FLOVENT HFA 44 mcg given as 88 mcg twice daily. FLOVENT HFA was delivered using an AeroChamber Plus VHC with a mask to subjects aged younger than 4 years. Data from adult subjects with asthma following FLOVENT HFA 110 mcg given as 220 mcg twice daily (n = 15) and following FLOVENT HFA 220 mcg given as 440 mcg twice daily (n = 17) at steady state were also included. Data for 22 subjects came from a single-dose crossover study of 264 mcg (6 doses of FLOVENT HFA 44 mcg) with and without AeroChamber Plus VHC in children with asthma aged 4 to 11 years.

Stratification of exposure data following FLOVENT HFA 88 mcg by age and study indicated that systemic exposure to fluticasone propionate at steady state was similar in children aged 6 to younger than 12 months, children aged 1 to younger than 4 years, and adults and adolescents aged 12 years and older. Exposure was lower in children aged 4 to 11 years, who did not use a VHC, as shown in Table 3.

Table 3. Systemic Exposure to Fluticasone Propionate following FLOVENT HFA 88 mcg Twice Daily
Age | Valved Holding Chamber | N | AUC(0-τ), pg•h/mL; (95% CI) | Cmax, pg/mL; (95% CI)
6 to <12 Months | Yes | 17 | 141 (88, 227) | 19 (13, 29)
1 to <4 Years | Yes | 164 | 143 (131, 157) | 20 (18, 21)
4 to 11 Years | No | 14 | 68 (48, 97) | 11 (8, 16)
≥12 Years | No | 20 | 149 (106, 210) | 20 (15, 27)

The lower exposure to fluticasone propionate in children aged 4 to 11 years who did not use a VHC may reflect the inability to coordinate actuation and inhalation of the metered-dose inhaler. The impact of the use of a VHC on exposure to fluticasone propionate in patients aged 4 to 11 years was evaluated in a single-dose crossover trial with FLOVENT HFA 44 mcg given as 264 mcg. In this trial, use of a VHC increased systemic exposure to fluticasone propionate (Table 4), possibly correcting for the inability to coordinate actuation and inhalation.

Table 4. Systemic Exposure to Fluticasone Propionate following a Single Dose of FLOVENT HFA 264 mcg
Age | Valved Holding Chamber | N | AUC(0-∞), pg•h/mL; (95% CI) | Cmax, pg/mL; (95% CI)
4 to 11 Years | Yes | 22 | 373 (297, 468) | 61 (51, 73)
4 to 11 Years | No | 21 | 141 (111, 178) | 23 (19, 28)

There was a dose-related increase in systemic exposure in subjects aged 12 years and older receiving higher doses of fluticasone propionate (220 and 440 mcg twice daily). The AUC(0-τ) in pg•h/mL was 358 (95% CI: 272, 473) and 640 (95% CI: 477, 858), and Cmax in pg/mL was 47.3 (95% CI: 37, 61) and 87 (95% CI: 68, 112) following fluticasone propionate 220 and 440 mcg, respectively.

Patients with Hepatic and Renal Impairment: Formal pharmacokinetic studies using FLOVENT HFA have not been conducted in patients with hepatic or renal impairment. However, since fluticasone propionate is predominantly cleared by hepatic metabolism, impairment of liver function may lead to accumulation of fluticasone propionate in plasma. Therefore, patients with hepatic disease should be closely monitored.

Racial or Ethnic Groups: No significant difference in clearance (CL/F) of fluticasone propionate in Caucasian, African‑American, Asian, or Hispanic populations was observed.

Drug Interaction Studies

Inhibitors of Cytochrome P450 3A4: Ritonavir: Fluticasone propionate is a substrate of CYP3A4. Coadministration of fluticasone propionate and the strong CYP3A4 inhibitor ritonavir is not recommended based upon a multiple-dose, crossover drug interaction trial in 18 healthy subjects. Fluticasone propionate aqueous nasal spray (200 mcg once daily) was coadministered for 7 days with ritonavir (100 mg twice daily). Plasma fluticasone propionate concentrations following fluticasone propionate aqueous nasal spray alone were undetectable (<10 pg/mL) in most subjects, and when concentrations were detectable, peak levels (Cmax) averaged 11.9 pg/mL (range: 10.8 to 14.1 pg/mL) and AUC(0-τ) averaged 8.43 pg•h/mL (range: 4.2 to 18.8 pg•h/mL). Fluticasone propionate Cmax and AUC(0-τ) increased to 318 pg/mL (range: 110 to 648 pg/mL) and 3,102.6 pg•h/mL (range: 1,207.1 to 5,662.0 pg•h/mL), respectively, after coadministration of ritonavir with fluticasone propionate aqueous nasal spray. This significant increase in plasma fluticasone propionate exposure resulted in a significant decrease (86%) in serum cortisol AUC.

Ketoconazole: In a placebo-controlled crossover trial in 8 healthy adult volunteers, coadministration of a single dose of orally inhaled fluticasone propionate (1,000 mcg) with multiple doses of ketoconazole (200 mg) to steady state resulted in increased plasma fluticasone propionate exposure, a reduction in plasma cortisol AUC, and no effect on urinary excretion of cortisol.

Following orally inhaled fluticasone propionate alone, AUC(2-last) averaged 1.559 ng•h/mL (range: 0.555 to 2.906 ng•h/mL) and AUC(2-∞) averaged 2.269 ng•h/mL (range: 0.836 to 3.707 ng•h/mL). Fluticasone propionate AUC(2-last) and AUC(2-∞) increased to 2.781 ng•h/mL (range: 2.489 to 8.486 ng•h/mL) and 4.317 ng•h/mL (range: 3.256 to 9.408 ng•h/mL), respectively, after coadministration of ketoconazole with orally inhaled fluticasone propionate. This increase in plasma fluticasone propionate concentration resulted in a decrease (45%) in serum cortisol AUC.

Erythromycin: In a multiple-dose drug interaction trial, coadministration of orally inhaled fluticasone propionate (500 mcg twice daily) and erythromycin (333 mg 3 times daily) did not affect fluticasone propionate pharmacokinetics.

13 NONCLINICAL TOXICOLOGY

13.1 Carcinogenesis, Mutagenesis, Impairment of Fertility

Fluticasone propionate demonstrated no tumorigenic potential in mice at oral doses up to 1,000 mcg/kg (approximately 3 and 10 times the MRHDID for adults and children aged 4 to 11 years, respectively, on a mcg/m^2 basis) for 78 weeks or in rats at inhalation doses up to 57 mcg/kg (approximately 0.3 times and approximately equivalent to the MRHDID for adults and children aged 4 to 11 years, respectively, on a mcg/m^2 basis) for 104 weeks.

Fluticasone propionate did not induce gene mutation in prokaryotic or eukaryotic cells in vitro. No significant clastogenic effect was seen in cultured human peripheral lymphocytes in vitro or in the in vivo mouse micronucleus test.

Fertility and reproductive performance were unaffected in male and female rats at subcutaneous doses up to 50 mcg/kg (approximately 0.3 times the MRHDID for adults on a mcg/m^2 basis).

14 CLINICAL STUDIES

14.1 Adult and Adolescent Subjects Aged 12 Years and Older

Three randomized, double-blind, parallel-group, placebo-controlled, U.S. clinical trials were conducted in 980 adult and adolescent subjects (aged 12 years and older) with asthma to assess the efficacy and safety of FLOVENT HFA in the treatment of asthma. Fixed dosages of 88, 220, and 440 mcg twice daily (each dose administered as 2 inhalations of the 44-, 110-, and 220-mcg strengths, respectively) and 880 mcg twice daily (administered as 4 inhalations of the 220-mcg strength) were compared with placebo to provide information about appropriate dosing to cover a range of asthma severity. Subjects in these trials included those inadequately controlled with bronchodilators alone (Trial 1), those already receiving ICS (Trial 2), and those requiring oral corticosteroid therapy (Trial 3). In all 3 trials, subjects were allowed to use VENTOLIN (albuterol, USP) Inhalation Aerosol as needed for relief of acute asthma symptoms. In Trials 1 and 2, other maintenance asthma therapies were discontinued.

Trial 1 enrolled 397 subjects with asthma inadequately controlled on bronchodilators alone. FLOVENT HFA was evaluated at dosages of 88, 220, and 440 mcg twice daily for 12 weeks. Baseline FEV1 values were similar across groups (mean 67% of predicted normal). All 3 dosages of FLOVENT HFA demonstrated a statistically significant improvement in lung function as measured by improvement in AM pre-dose FEV1 compared with placebo. This improvement was observed after the first week of treatment and was maintained over the 12-week treatment period.

At Endpoint (last observation), mean change from baseline in AM pre-dose percent predicted FEV1 was greater in all 3 groups treated with FLOVENT HFA (9.0% to 11.2%) compared with the placebo group (3.4%). The mean differences between the groups treated with FLOVENT HFA 88, 220, and 440 mcg and the placebo group were statistically significant, and the corresponding 95% confidence intervals were (2.2%, 9.2%), (2.8%, 9.9%), and (4.3%, 11.3%), respectively.

Figure 1 displays results of pulmonary function tests (mean percent change from baseline in FEV1 prior to AM dose) for the recommended starting dosage of FLOVENT HFA (88 mcg twice daily) and placebo from Trial 1. This trial used predetermined criteria for lack of efficacy (indicators of worsening asthma), resulting in withdrawal of more subjects in the placebo group. Therefore, pulmonary function results at Endpoint (the last evaluable FEV1 result, including most subjects’ lung function data) are also displayed.

Figure 1. A 12-Week Clinical Trial in Subjects Aged 12 Years and Older Inadequately Controlled on Bronchodilators Alone: Mean Percent Change from Baseline in FEV1 Prior to AM Dose (Trial 1)

In Trial 2, FLOVENT HFA at dosages of 88, 220, and 440 mcg twice daily was evaluated over 12 weeks of treatment in 415 subjects with asthma who were already receiving an ICS at a daily dose within its recommended dose range in addition to as-needed albuterol. Baseline FEV1 values were similar across groups (mean 65% to 66% of predicted normal). All 3 dosages of FLOVENT HFA demonstrated a statistically significant improvement in lung function, as measured by improvement in FEV1, compared with placebo. This improvement was observed after the first week of treatment and was maintained over the 12-week treatment period. Discontinuations from the trial for lack of efficacy (defined by a pre-specified decrease in FEV1 or PEF, or an increase in use of VENTOLIN or nighttime awakenings requiring treatment with VENTOLIN) were lower in the groups treated with FLOVENT HFA (6% to 11%) compared with placebo (50%).

At Endpoint (last observation), mean change from baseline in AM pre-dose percent predicted FEV1 was greater in all 3 groups treated with FLOVENT HFA (2.2% to 4.6%) compared with the placebo group (-8.3%). The mean differences between the groups treated with FLOVENT HFA 88, 220, and 440 mcg and the placebo group were statistically significant, and the corresponding 95% confidence intervals were (7.1%, 13.8%), (8.2%, 14.9%), and (9.6%, 16.4%), respectively.

Figure 2 displays the mean percent change from baseline in FEV1 from Week 1 through Week 12. This trial also used predetermined criteria for lack of efficacy, resulting in withdrawal of more subjects in the placebo group; therefore, pulmonary function results at Endpoint are also displayed.

Figure 2. A 12-Week Clinical Trial in Subjects Aged 12 Years and Older Already Receiving Daily Inhaled Corticosteroids: Mean Percent Change from Baseline in FEV1 Prior to AM Dose (Trial 2)

In both trials, use of VENTOLIN, AM and PM PEF, and asthma symptom scores showed numerical improvement with FLOVENT HFA compared with placebo.

Trial 3 enrolled 168 subjects with asthma requiring oral prednisone therapy (average baseline daily prednisone dose ranged from 13 to 14 mg). FLOVENT HFA at dosages of 440 and 880 mcg twice daily was evaluated over a 16-week treatment period. Baseline FEV1 values were similar across groups (mean 59% to 62% of predicted normal). Over the course of the trial, subjects treated with either dosage of FLOVENT HFA required a statistically significantly lower mean daily oral prednisone dose (6 mg) compared with placebo-treated subjects (15 mg). Both dosages of FLOVENT HFA enabled a larger percentage of subjects (59% and 56% in the groups treated with FLOVENT HFA 440 and 880 mcg, respectively, twice daily) to eliminate oral prednisone as compared with placebo (13%) (see Figure 3). There was no efficacy advantage of FLOVENT HFA 880 mcg twice daily compared with 440 mcg twice daily. Accompanying the reduction in oral corticosteroid use, subjects treated with either dosage of FLOVENT HFA had statistically significantly improved lung function, fewer asthma symptoms, and less use of VENTOLIN Inhalation Aerosol compared with the placebo-treated subjects.

Figure 3. A 16-Week Clinical Trial in Subjects Aged 12 Years and Older Requiring Chronic Oral Prednisone Therapy: Change in Maintenance Prednisone Dose

Two long-term safety trials (Trial 4 and Trial 5) of ≥6 months’ duration were conducted in 507 adult and adolescent subjects with asthma. Trial 4 was designed to monitor the safety of 2 doses of FLOVENT HFA, while Trial 5 compared fluticasone propionate HFA with fluticasone propionate CFC. Trial 4 enrolled 182 subjects who were treated daily with low to high doses of ICS, beta-agonists (short-acting [as needed or regularly scheduled] or long-acting), theophylline, inhaled cromolyn or nedocromil sodium, leukotriene receptor antagonists, or 5-lipoxygenase inhibitors at baseline. FLOVENT HFA at dosages of 220 and 440 mcg twice daily was evaluated over a 26-week treatment period in 89 and 93 subjects, respectively. Trial 5 enrolled 325 subjects who were treated daily with moderate to high doses of ICS, with or without concurrent use of salmeterol or albuterol, at baseline. Fluticasone propionate HFA at a dosage of 440 mcg twice daily and fluticasone propionate CFC at a dosage of 440 mcg twice daily were evaluated over a 52-week treatment period in 163 and 162 subjects, respectively. Baseline FEV1 values were similar across groups (mean 81% to 84% of predicted normal). Throughout the 52-week treatment period, asthma control was maintained with both formulations of fluticasone propionate compared with baseline. In both trials, none of the subjects were withdrawn due to lack of efficacy.

14.2 Pediatric Subjects Aged 4 to 11 Years

A 12-week clinical trial conducted in 241 pediatric subjects with asthma was supportive of efficacy but inconclusive due to measurable levels of fluticasone propionate in 6/48 (13%) of the plasma samples from subjects randomized to placebo. Efficacy in subjects aged 4 to 11 years is extrapolated from adult data with FLOVENT HFA and other supporting data [see Use in Specific Populations (8.4)].

16 HOW SUPPLIED/STORAGE AND HANDLING

FLOVENT HFA is supplied in the following boxes of 1 as a pressurized aluminum canister fitted with a counter and supplied with a dark orange actuator with a peach cap:

- FLOVENT HFA 44 mcg: 10.6-g canister containing 120 actuations (NDC 68788-6926-1)

Each inhaler is packaged with a Patient Information leaflet.

The dark orange actuator supplied with FLOVENT HFA should not be used with any other product canisters, and actuators from other products should not be used with a FLOVENT HFA canister.

Counter

FLOVENT HFA has a counter attached to the canister. The counter starts at 124 and counts down each time a spray is released. The correct amount of medication in each actuation cannot be assured after the counter reads 000, even though the canister is not completely empty and will continue to operate. The inhaler should be discarded when the counter reads 000.

Contents under Pressure

Do not puncture. Do not use or store near heat or open flame. Exposure to temperatures above 120°F may cause bursting. Never throw canister into fire or incinerator.

Storage

Store at room temperature between 68°F and 77°F (20°C and 25°C); excursions permitted from 59°F to 86°F (15°C to 30°C) [See USP Controlled Room Temperature]. Store the inhaler with the mouthpiece down. For best results, the inhaler should be at room temperature before use.

17 PATIENT COUNSELING INFORMATION

Advise the patient to read the FDA-approved patient labeling (Patient Information and Instructions for Use).

Oropharyngeal Candidiasis

Inform patients that localized infections with Candida albicans occurred in the mouth and pharynx in some patients. If oropharyngeal candidiasis develops, treat it with appropriate local or systemic (i.e., oral) antifungal therapy while still continuing therapy with FLOVENT HFA, but at times therapy with FLOVENT HFA may need to be temporarily interrupted under close medical supervision. Advise patients to rinse the mouth with water without swallowing after inhalation to help reduce the risk of thrush. [See Warnings and Precautions (5.1).]

Status Asthmaticus and Acute Asthma Symptoms

Inform patients that FLOVENT HFA is not a bronchodilator and is not intended for use as rescue medicine for acute asthma exacerbations. Advise patients to treat acute asthma symptoms with an inhaled, short-acting beta2-agonist such as albuterol. Instruct patients to contact their physicians immediately if there is deterioration of their asthma. [See Warnings and Precautions (5.2).]

Immunosuppression and Risk of Infections

Warn patients who are on immunosuppressant doses of corticosteroids to avoid exposure to chickenpox or measles and, if exposed, to consult their physicians without delay. Inform patients of potential worsening of existing tuberculosis; fungal, bacterial, viral, or parasitic infections; or ocular herpes simplex. [See Warnings and Precautions (5.3).]

Hypercorticism and Adrenal Suppression

Advise patients that FLOVENT HFA may cause systemic corticosteroid effects of hypercorticism and adrenal suppression. Additionally, inform patients that deaths due to adrenal insufficiency have occurred during and after transfer from systemic corticosteroids. Patients should taper slowly from systemic corticosteroids if transferring to FLOVENT HFA. [See Warnings and Precautions (5.5).]

Hypersensitivity Reactions, including Anaphylaxis

Advise patients that immediate hypersensitivity reactions (e.g., urticaria, angioedema, rash, bronchospasm, hypotension), including anaphylaxis, may occur after administration of FLOVENT HFA. Patients should discontinue FLOVENT HFA if such reactions occur. [See Warnings and Precautions (5.6).]

Reduction in Bone Mineral Density

Advise patients who are at an increased risk for decreased BMD that the use of corticosteroids may pose an additional risk. [See Warnings and Precautions (5.7).]

Reduced Growth Velocity

Inform patients that orally inhaled corticosteroids, including FLOVENT HFA, may cause a reduction in growth velocity when administered to pediatric patients. Physicians should closely follow the growth of children and adolescents taking corticosteroids by any route. [See Warnings and Precautions (5.8).]

Glaucoma and Cataracts

Advise patients that long-term use of ICS may increase the risk of some eye problems (cataracts or glaucoma); consider regular eye examinations. [See Warnings and Precautions (5.9).]

Use Daily for Best Effect

Patients should use FLOVENT HFA at regular intervals as directed. Individual patients will experience a variable time to onset and degree of symptom relief and the full benefit may not be achieved until treatment has been administered for 1 to 2 weeks or longer. Patients should not increase the prescribed dosage but should contact their physicians if symptoms do not improve or if the condition worsens. Instruct patients not to stop use of FLOVENT HFA abruptly. Patients should contact their physicians immediately if they discontinue use of FLOVENT HFA.

Trademarks are owned by or licensed to the GSK group of companies. The other brands listed are trademarks owned by or licensed to their respective owners and are not owned by or licensed to the GSK group of companies. The makers of these brands are not affiliated with and do not endorse the GSK group of companies or its products.

GlaxoSmithKline

Durham, NC 27701

©2023 GSK group of companies or its licensor.

FLH:14PI

PATIENT INFORMATION

FLOVENT (FLO vent) HFA

(fluticasone propionate inhalation aerosol)

for oral inhalation use

What is FLOVENT HFA?

FLOVENT HFA is a prescription inhaled corticosteroid (ICS) medicine used for the long-term treatment of asthma in people aged 4 years and older.

- ICS medicines such as fluticasone propionate help to decrease inflammation in the lungs. Inflammation in the lungs can lead to breathing problems.
- FLOVENT HFA is not used to relieve sudden breathing problems and will not replace a rescue inhaler.
- It is not known if FLOVENT HFA is safe and effective in children younger than 4 years of age.

Do not use FLOVENT HFA:

- to relieve sudden breathing problems.
- as a rescue inhaler.
- if you are allergic to fluticasone propionate or any of the ingredients in FLOVENT HFA. See the end of this leaflet for a complete list of ingredients in FLOVENT HFA.

Before using FLOVENT HFA, tell your healthcare provider about all of your medical conditions, including if you:

- have liver problems.
- have weak bones (osteoporosis).
- have an immune system problem.
- have or have had eye problems such as glaucoma, increased pressure in your eye, cataracts, or other changes in vision.
- have any type of viral, bacterial, or fungal infection.
- are exposed to chickenpox or measles.
- are pregnant or plan to become pregnant. It is not known if FLOVENT HFA may harm your unborn baby.
- are breastfeeding. It is not known if the medicine in FLOVENT HFA passes into your milk and if it can harm your baby.

Tell your healthcare provider about all the medicines you take, including prescription and over-the-counter medicines, vitamins, and herbal supplements. FLOVENT HFA and certain other medicines may interact with each other. This may cause serious side effects. Especially tell your healthcare provider if you take antifungal or anti-HIV medicines.

Know the medicines you take. Keep a list of them to show your healthcare provider and pharmacist when you get a new medicine.

How should I use FLOVENT HFA?

Read the step-by-step instructions for using FLOVENT HFA at the end of this Patient Information.

- Do not use FLOVENT HFA unless your healthcare provider has taught you how to use the inhaler and you understand how to use it correctly.
- Children should use FLOVENT HFA with an adult’s help, as instructed by the child’s healthcare provider.
- FLOVENT HFA comes in 3 different strengths. Your healthcare provider prescribed the strength that is best for you.
- Use FLOVENT HFA exactly as your healthcare provider tells you to use it. Do not use FLOVENT HFA more often than prescribed.
- It may take 1 to 2 weeks or longer after you start FLOVENT HFA for your asthma symptoms to get better. You must use FLOVENT HFA regularly.
- Do not stop using FLOVENT HFA, even if you are feeling better, unless your healthcare provider tells you to.
- If you miss a dose of FLOVENT HFA, just skip that dose. Take your next dose at your usual time. Do not take 2 doses at 1 time.
- FLOVENT HFA does not relieve sudden breathing problems. Always have a rescue inhaler with you to treat sudden symptoms. If you do not have a rescue inhaler, call your healthcare provider to have one prescribed for you.
- Rinse your mouth with water without swallowing after each dose of FLOVENT HFA. This will help lessen the chance of getting a yeast infection (thrush) in your mouth and throat.
- Call your healthcare provider or get medical care right away if:
  - your breathing problems get worse.
  - you need to use your rescue inhaler more often than usual.
  - your rescue inhaler does not work as well to relieve your symptoms.
  - you need to use 4 or more inhalations of your rescue inhaler in 24 hours for 2 or more days in a row.
  - you use 1 whole canister of your rescue inhaler in 8 weeks.
  - your peak flow meter results decrease. Your healthcare provider will tell you the numbers that are right for you.

What are the possible side effects of FLOVENT HFA?

FLOVENT HFA can cause serious side effects, including:

- fungal infection in your mouth or throat (thrush). Rinse your mouth with water without swallowing after using FLOVENT HFA to help reduce your chance of getting thrush.
- weakened immune system and increased chance of getting infections (immunosuppression).
- reduced adrenal function (adrenal insufficiency). Adrenal insufficiency is a condition where the adrenal glands do not make enough steroid hormones. This can happen when you stop taking oral corticosteroid medicines (such as prednisone) and start taking a medicine containing an inhaled steroid (such as FLOVENT HFA). During this transition period, when your body is under stress such as from fever, trauma (such as a car accident), infection, or surgery, adrenal insufficiency can get worse and may cause death.
Symptoms of adrenal insufficiency include:
ο feeling tired ο nausea and vomiting
ο lack of energy ο low blood pressure (hypotension)
ο weakness
- serious allergic reactions. Call your healthcare provider or get emergency medical care if you get any of the following symptoms of a serious allergic reaction:
ο rash ο swelling of your face, mouth, and tongue
ο hives ο breathing problems
- bone thinning or weakness (osteoporosis).
- slowed growth in children. Your child’s growth should be checked regularly by the healthcare provider while using FLOVENT HFA.
- eye problems including glaucoma, increased pressure in your eye, cataracts, or other changes in vision. You should have regular eye exams while using FLOVENT HFA.
- increased wheezing (bronchospasm). Increased wheezing can happen right away after using FLOVENT HFA. Always have a rescue inhaler with you to treat sudden wheezing.

Common side effects of FLOVENT HFA include:

• upper respiratory tract infection • diarrhea • cough
• throat irritation • difficulty speaking • persistent cough
• headache • sinus irritation

These are not all the possible side effects of FLOVENT HFA.

Call your doctor for medical advice about side effects. You may report side effects to FDA at 1-800-FDA-1088.

How should I store FLOVENT HFA?

- Store FLOVENT HFA at room temperature between 68°F and 77°F (20°C and 25°C) with the mouthpiece down.
- The contents of your FLOVENT HFA inhaler are under pressure. Do not puncture. Do not use or store near heat or open flame. Temperatures above 120°F may cause the canister to burst.
- Do not throw into fire or an incinerator.
- Safely throw away FLOVENT HFA in the trash when the counter reads 000.

Keep FLOVENT HFA and all medicines out of the reach of children.

General information about the safe and effective use of FLOVENT HFA.

Medicines are sometimes prescribed for purposes other than those listed in a Patient Information leaflet. Do not use FLOVENT HFA for a condition for which it was not prescribed. Do not give FLOVENT HFA to other people, even if they have the same symptoms that you have. It may harm them.

You can ask your healthcare provider or pharmacist for information about FLOVENT HFA that was written for health professionals.

What are the ingredients in FLOVENT HFA?

Active ingredient: fluticasone propionate

Inactive ingredient: propellant HFA-134a

For more information about FLOVENT HFA, call 1-888-825-5249.

Trademarks are owned by or licensed to the GSK group of companies.

GlaxoSmithKline, Durham, NC 27701

©2023 GSK group of companies or its licensor.

FLH:10PIL

This Patient Information has been approved by the U.S. Food and Drug Administration. Revised: September 2023

INSTRUCTIONS FOR USE

FLOVENT (FLO vent) HFA

(fluticasone propionate inhalation aerosol)

for oral inhalation use

Your FLOVENT HFA inhaler

Figure A

- The metal canister holds the medicine. See Figure A.
- The metal canister has a counter to show how many sprays of medicine you have left. The number shows through a window in the back of the dark orange plastic actuator. See Figure A.

- The counter starts at 124. The number will count down by 1 each time you spray the inhaler. The counter will stop counting at 000.
- Do not try to change the numbers or take the counter off the metal canister. The counter cannot be reset, and it is permanently attached to the metal canister.
- The dark orange plastic actuator sprays the medicine from the metal canister. The plastic actuator has a peach protective cap that covers the mouthpiece. See Figure A. Keep the protective cap on the mouthpiece when the metal canister is not in use.
- Do not use the plastic actuator with a canister of medicine from any other inhaler.
- Do not use a FLOVENT HFA metal canister with an actuator from any other inhaler.

Before using your FLOVENT HFA inhaler

- The inhaler should be at room temperature before you use it.
- If a child needs help using the inhaler, an adult should help the child use the inhaler with or without a valved holding chamber, which may also be attached to a mask. The adult should follow the instructions that came with the valved holding chamber. An adult should watch a child use the inhaler to be sure it is used correctly.

Priming your FLOVENT HFA inhaler

Figure B

Figure C

Figure D

Before you use FLOVENT HFA for the first time, you must prime the inhaler so that you will get the right amount of medicine when you use it.

- To take the cap off the mouthpiece, squeeze the sides of the cap and pull it straight out. See Figure B.
- Shake the inhaler well for 5 seconds.
- Spray the inhaler 1 time into the air away from your face. Avoid spraying in eyes. See Figure C.
- Shake and spray the inhaler like this 3 more times to finish priming it. The counter should now read 120. See Figure D.
- You must prime your inhaler again if you have not used it in more than 7 days or if you have dropped it. To take the cap off the mouthpiece, squeeze the sides of the cap and pull it straight out. Shake the inhaler well for 5 seconds. Then spray it 1 time into the air away from your face.

How to use your FLOVENT HFA inhaler

Follow these steps every time you use FLOVENT HFA.

Figure E

Figure F

Figure G

Figure H

Step 1. Make sure the metal canister fits firmly in the plastic actuator. The counter should show through the window in the plastic actuator.
To take the cap off the mouthpiece, squeeze the sides of the cap and pull it straight out.
Look inside the mouthpiece for foreign objects and take out any you see.
Step 2. Hold the inhaler with the mouthpiece down and shake it well for 5 seconds. See Figure E.
Step 3. Breathe out through your mouth and push as much air from your lungs as you can. See Figure F.
Step 4. Put the mouthpiece in your mouth and close your lips around it. Push the top of the metal canister firmly all the way down while you breathe in deeply and slowly through your mouth. See Figure G.
Step 5. After the spray comes out, take your finger off the metal canister. After you have breathed in all the way, take the inhaler out of your mouth and close your mouth.
Step 6. Hold your breath for about 10 seconds, or for as long as is comfortable. Breathe out slowly as long as you can.

Wait about 30 seconds and shake the inhaler well for 5 seconds. Repeat Step 2 through Step 6.
Step 7. Rinse your mouth with water after breathing in the medicine. Spit out the water. Do not swallow it. See Figure H.
Step 8. Put the cap back on the mouthpiece after you finish using the inhaler. Make sure it snaps firmly into place.

Cleaning your FLOVENT HFA inhaler

Figure I

Figure J

Clean your inhaler at least 1 time each week after your evening dose. You may not see any medicine build-up on the inhaler, but it is important to keep it clean so medicine build-up will not block the spray. See Figure I.

Step 9. Take the cap off the mouthpiece by squeezing the sides of the cap and pulling it straight out. Do not take the metal canister out of the plastic actuator.
Step 10. Use a clean cotton swab dampened with water to clean the small circular opening where the medicine sprays out of the metal canister. Gently twist the swab in a circular motion to take off any medicine. See Figure J. Repeat with a new swab dampened with water to take off any medicine still at the opening.
Step 11. Wipe the inside of the mouthpiece with a clean tissue dampened with water. Let the plastic actuator air-dry overnight.
Step 12. Put the cap back on the mouthpiece after the plastic actuator has dried.

Replacing your FLOVENT HFA inhaler

- When the counter reads 020, you should refill your prescription or ask your healthcare provider if you need another prescription for FLOVENT HFA.
- When the counter reads 000, throw the inhaler away. You should not keep using the inhaler when the counter reads 000 because you may not receive the right amount of medicine.
- Do not use the inhaler after the expiration date, which is on the packaging it comes in.

For correct use of your FLOVENT HFA inhaler, remember:

- The metal canister should always fit firmly in the plastic actuator.
- Shake the inhaler well for 5 seconds before each spray.
- Breathe in deeply and slowly to make sure you get all the medicine.
- Hold your breath for about 10 seconds after breathing in the medicine. Then breathe out fully.
- After each dose, rinse your mouth with water and spit it out. Do not swallow the water.
- Do not take the inhaler apart.
- Always keep the protective cap on the mouthpiece when your inhaler is not in use.
- Always store your inhaler with the mouthpiece pointing down.
- Clean your inhaler at least 1 time each week.

For more information about FLOVENT HFA or how to use your inhaler, call 1-888-825-5249.

Trademarks are owned by or licensed to the GSK group of companies.

GlaxoSmithKline, Durham, NC 27701

©2023 GSK group of companies or its licensor.

FLH:7IFU

This Instructions for Use has been approved by the U.S. Food and Drug Administration Revised: September 2023
Relabeled By: Preferred Pharmaceuticals Inc.

PACKAGE LABEL

PRINCIPAL DISPLAY PANEL

NDC 68788-6926-1

Flovent HFA

(fluticasone propionate inhalation aerosol)

44 mcg

For oral inhalation with FLOVENT HFA actuator only.

Attention Pharmacist: Detach Patient Information leaflet from package insert and dispense with inhaler.

See prescribing information for dosage information.

Rx only

Net Wt. 10.6 g

120 Metered Actuations

gsk

©2021 GSK group of companies or its licensor.

Relabeled By: Preferred Pharmaceuticals Inc.

Made in Singapore

62000000062556 Rev. 5/21